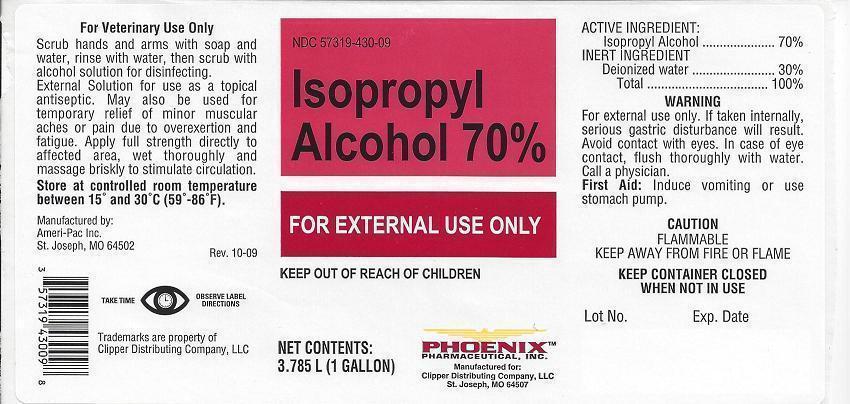 DRUG LABEL: Isopropyl Alcohol
NDC: 57319-430 | Form: LIQUID
Manufacturer: Phoenix Pharmaceutical Inc./ Clipper Distributing, Inc.
Category: animal | Type: OTC ANIMAL DRUG LABEL
Date: 20130917

ACTIVE INGREDIENTS: ISOPROPYL ALCOHOL 70 mL/100 mL
INACTIVE INGREDIENTS: WATER

Isopropyl Alcohol 70%

NDC 57319-430-09 Isopropyl Alcohol 70% FOR EXTERNAL USE ONLY KEEP OUT OF REACH OF CHILDREN

NET CONTENTS:

3.785L (1 GALLON)

PHOENIXTM

PHARMACEUTICAL, INC.

Manufactured for:

Clipper Distributing Company, LLC

St. Joseph, MO 64507

For Veterinary Use Only

Scrub hands and arms with soap and water, rinse with water, then scrub with alcohol solution for disinfecting.

External Solution for use as a topical antiseptic. may also be used for temporary relief of minor muscular aches or pain due to overexertion and fatigue. Apply full strength directly to affected area, wet thoroughly and massage briskly to stimulate circulation.

Store at controlled room temperature between 15° and 30°C (59°-86°F).

Manufactured by:
Ameri-Pac Inc.
St. Joseph, MO 64502

Rev. 10-09

TAKE TIME OBSERVE LABEL DIRECTIONS

Trademarks are property of
Clipper Distributing Company, LLC

ACTIVE INGREDIENT:

Isopropyl Alcohol ................ 70%

INERT INGREDIENT

Deionized Water ................. 30%
Total ................................. 100%

WARNING

For external use only. If taken internally, serious gastric disturbance will result. Avoid contact with eyes. In case of eye contact, flush thoroughly with water. Call a physician.

First Aid:

Induce vomiting or use stomach pump.

CAUTION

FLAMMABLE
KEEP AWAY FROM FIRE OR FLAME

KEEP CONTAINER CLOSED WHEN NOT IN USE